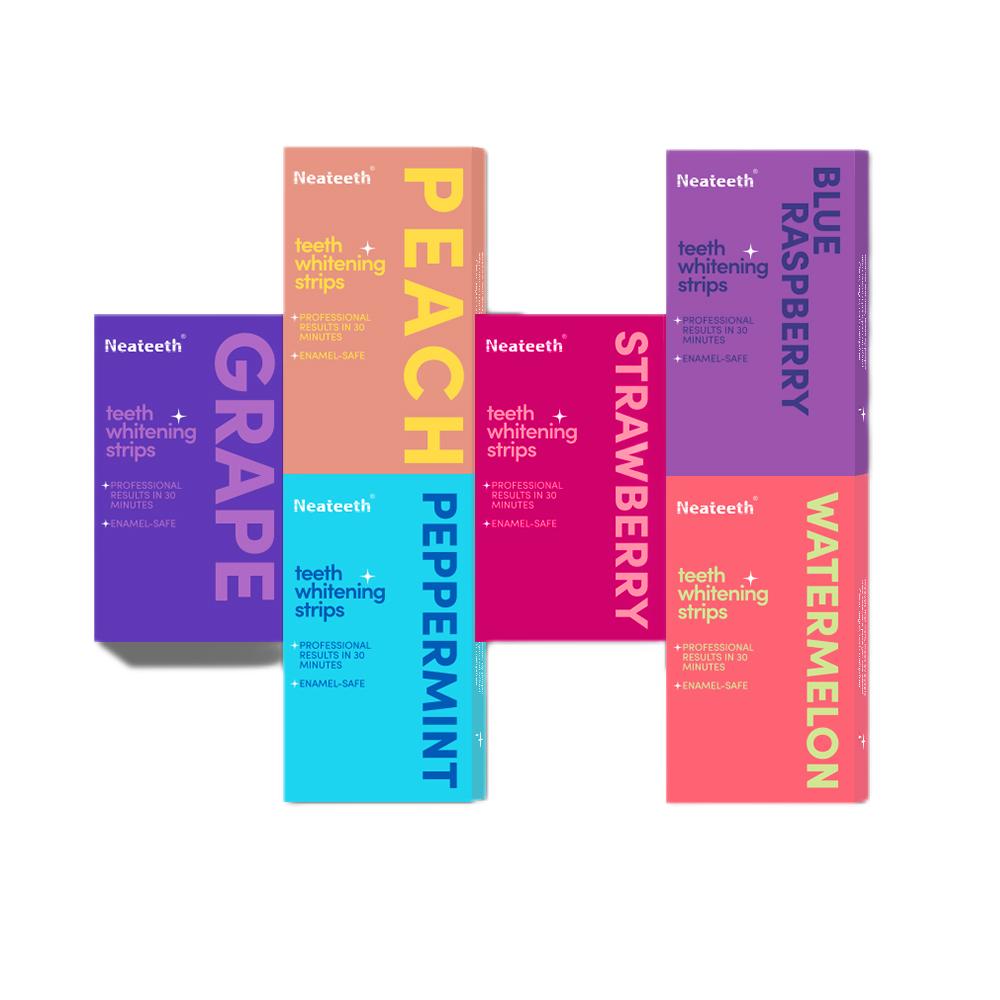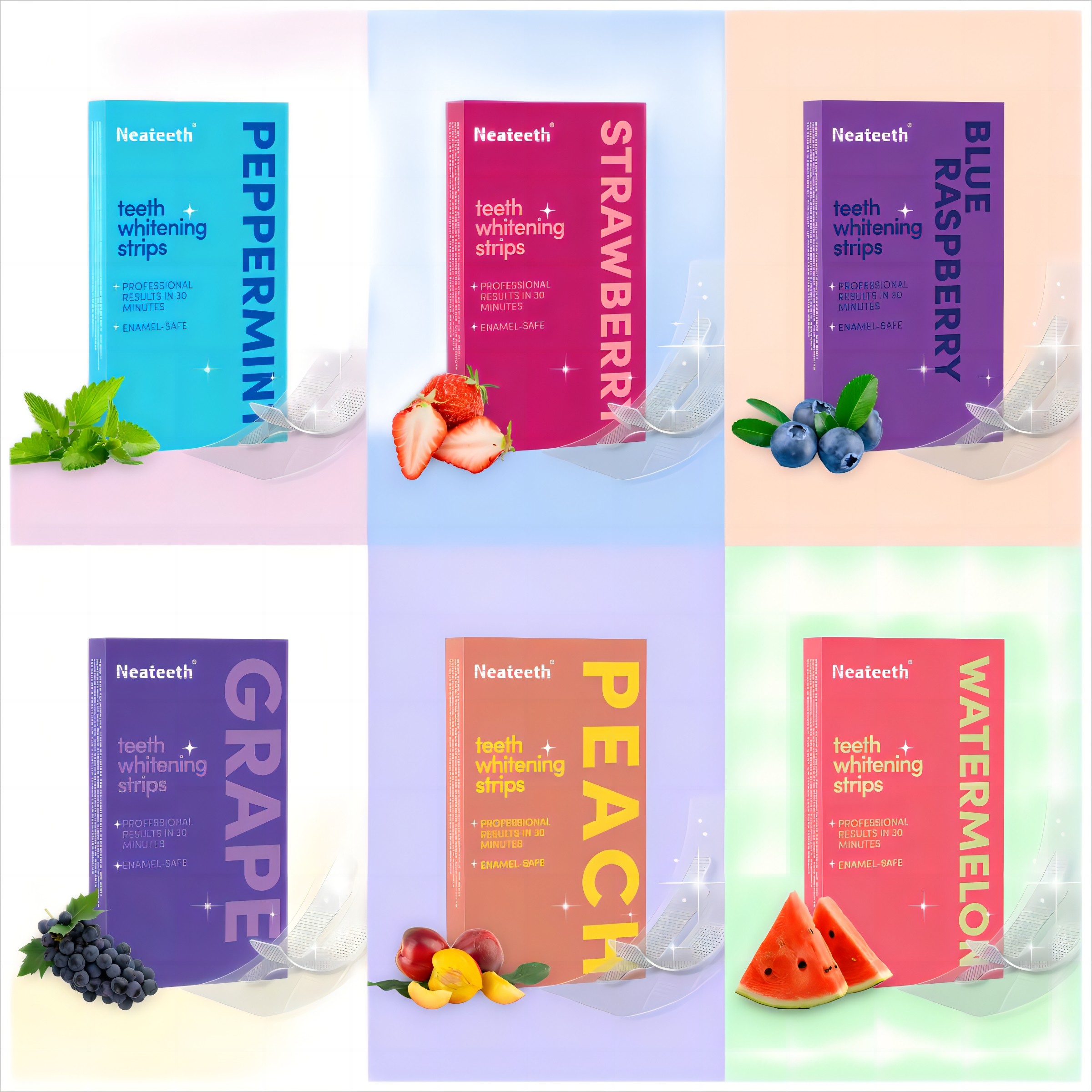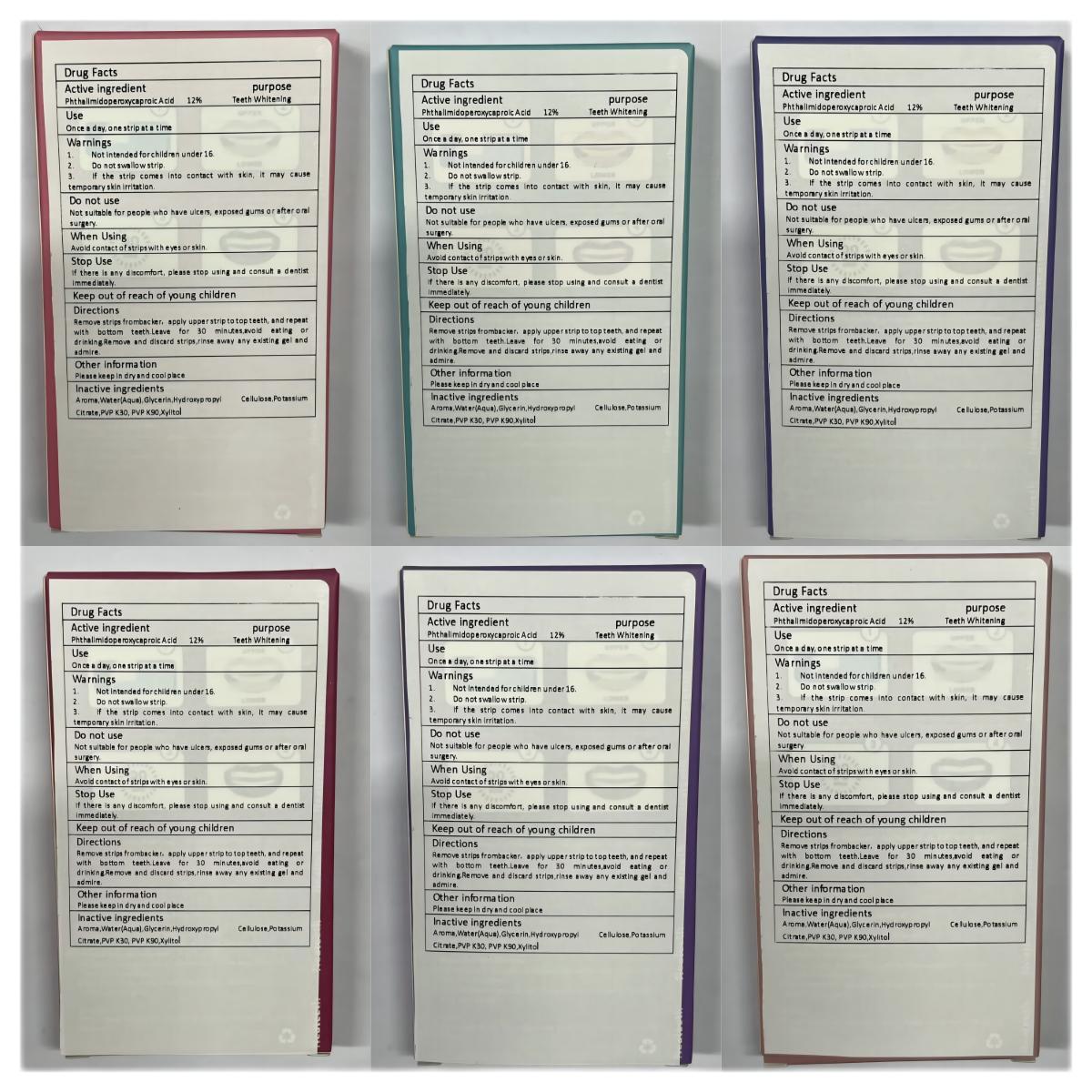 DRUG LABEL: Neateeth Teeth Whitening Strips
NDC: 83778-006 | Form: PATCH
Manufacturer: Nanchang Dental Bright Technology Co.,Ltd.
Category: otc | Type: HUMAN OTC DRUG LABEL
Date: 20231221

ACTIVE INGREDIENTS: PHTHALIMIDOPEROXYCAPROIC ACID 12 g/100 1
INACTIVE INGREDIENTS: HYDROXYPROPYL CELLULOSE, UNSPECIFIED; POVIDONE K30; XYLITOL; POVIDONE K90; WATER; GLYCERIN; POTASSIUM CITRATE

Active Ingredient

Phthalimidoperoxycaproic Acid 12%

Purpose

Teeth Whitening

Use

Once a day, one strip at a time

Warnings

1.Not intended for children under 16.

2.Do not swallow strip.

3.If the strip comes into contact with skin, it may cause temporary skin irritation.

Do not use

Not suitable for people who have ulcers, exposed gums or after oral surgery.

When Using

Avoid contact of strips with eyes or skin.

Stop Use

If there is any discomfort, please stop using and consult a dentist immediately.

Keep Oot Of Reach Of Children

Keep out of reach of young children

Directions

Remove strips frombacker，apply upper strip to top teeth, and repeat with bottom teeth.Leave for 30 minutes,avoid eating or drinking.Remove and discard strips,rinse away any existing gel and admire.

Other information

Please keep in dry and cool place

Inactive ingredients

Aroma,Water(Aqua),Glycerin,Hydroxypropyl Cellulose,Potassium Citrate,PVP K30,PVP K90,Xylitol